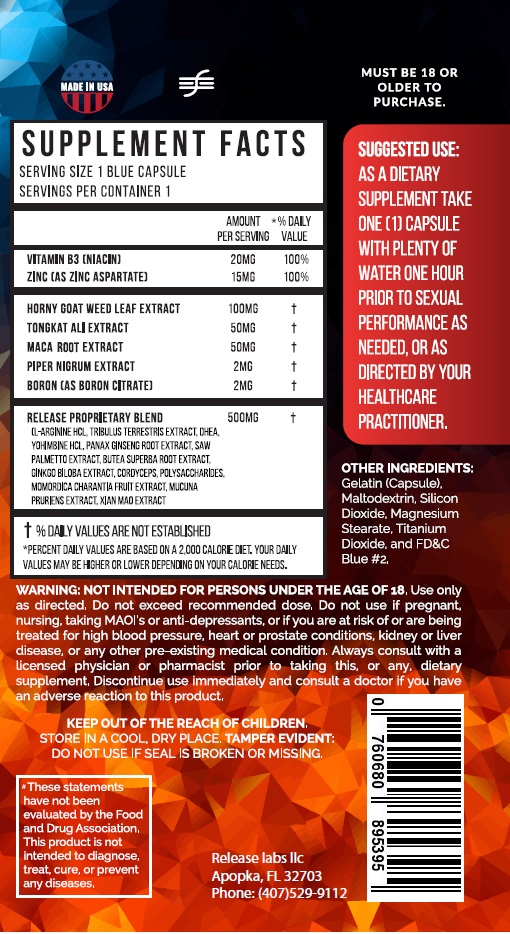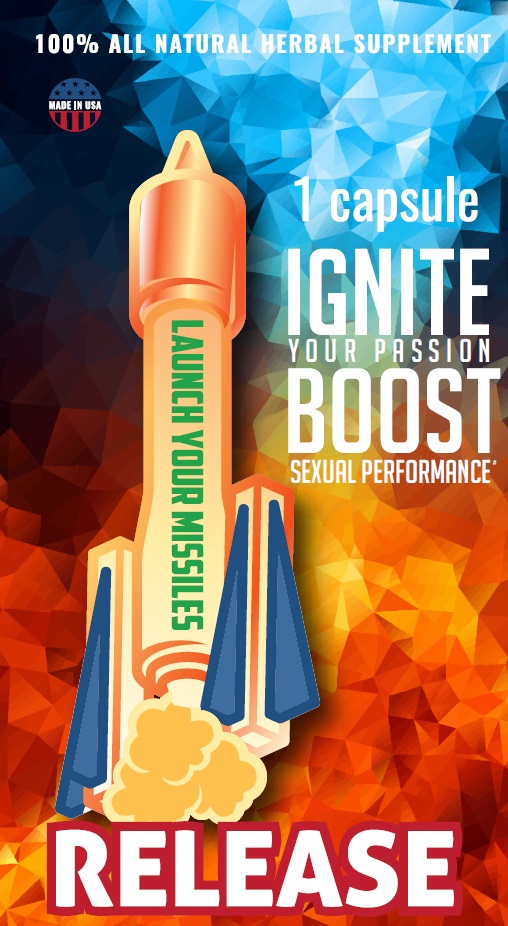 DRUG LABEL: IGNITE YOUR PASSION
NDC: 71724-200 | Form: CAPSULE
Manufacturer: FLPHARMACEUTICALS LLC
Category: other | Type: DIETARY SUPPLEMENT
Date: 20190215

ACTIVE INGREDIENTS: NIACIN 30 mg/1 1; ZINC ASPARTATE 15 mg/1 1; EPIMEDIUM GRANDIFLORUM TOP 175 mg/1 1; EURYCOMA LONGIFOLIA ROOT 40 mg/1 1; LEPIDIUM MEYENII ROOT 60 mg/1 1; WHITE PEPPER 5 mg/1 1; BORON CITRATE 2.5 mg/1 1; ARGININE HYDROCHLORIDE 100 mg/1 1; TRIBULUS TERRESTRIS 50 mg/1 1; ASIAN GINSENG 40 mg/1 1; SAW PALMETTO 25 mg/1 1; BUTEA SUPERBA ROOT 40 mg/1 1; GINKGO 40 mg/1 1; OPHIOCORDYCEPS SINENSIS 10 mg/1 1; MOMORDICA CHARANTIA FRUIT 15 mg/1 1; MUCUNA PRURIENS SEED 50 mg/1 1; PTYCHOPETALUM OLACOIDES ROOT 40 mg/1 1; CURCULIGO ORCHIOIDES ROOT 25 mg/1 1
INACTIVE INGREDIENTS: MALTODEXTRIN; SILICON DIOXIDE; MAGNESIUM STEARATE; GELATIN; TITANIUM DIOXIDE; FD&C BLUE NO. 2

IGNITE YOUR PASSION

STATEMENT OF IDENTITY

These statements have not been evaluated by the Food and Drug Administration.

HEALTH CLAIM

This product is not intended to diagnose, treat, cure, or prevent any disease.

WARNINGS

Use only as directed. Do not exceed recommended dosage. Do not use if tamper-resistant seal is broken or missing.

Must be 18 or older to purchase.

Do not use if pregnant, nursing, taking MAOI's or anti-depressants, or if you are at risk of or are being treated for high blood pressure, heart or prostate conditions, kidney or liver disease, or any other pre-existing medical condition. Always consult with a licensed physician or pharmacist prior to taking this, or any, dietary supplement.

Discontinue use immediately and consult a doctor if you have an adverse reaction to this product.

SAFE HANDLING WARNING

Store at room temperature in a cool, dry place. Do not use if seal broken or missing.

KEEP OUT OF REACH OF CHILDREN. NOT INTENDED FOR PERSONS UNDER THE AGE OF 18.

DOSAGE AND ADMINISTRATION

SUGGESTED USE: As a dietary supplement, take 1 capsule with plenty of water one hour prior to sexual performance as needed, or as directed by your Healthcare Practitioner.